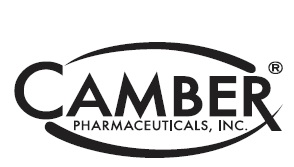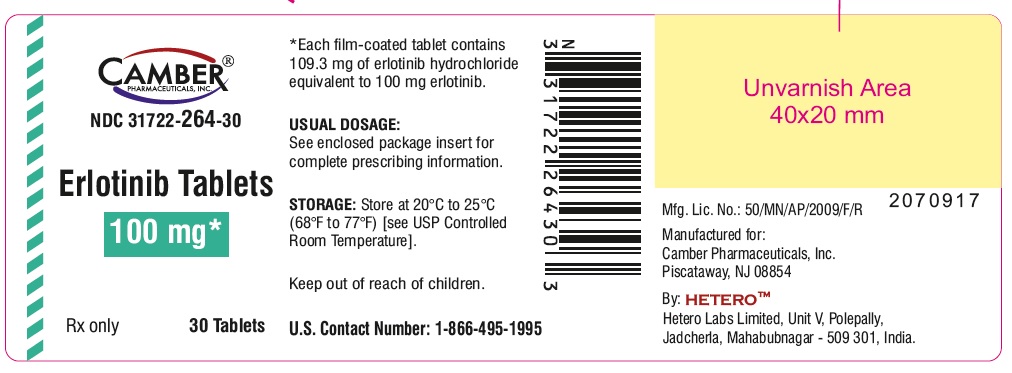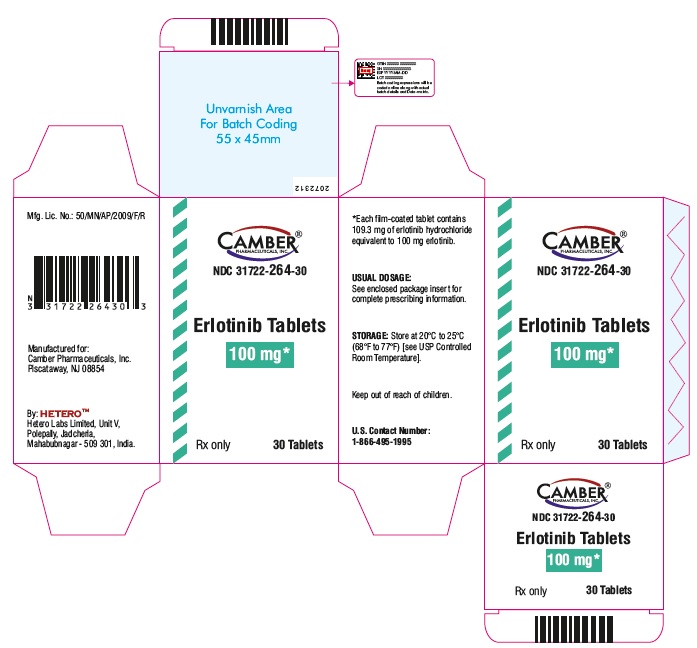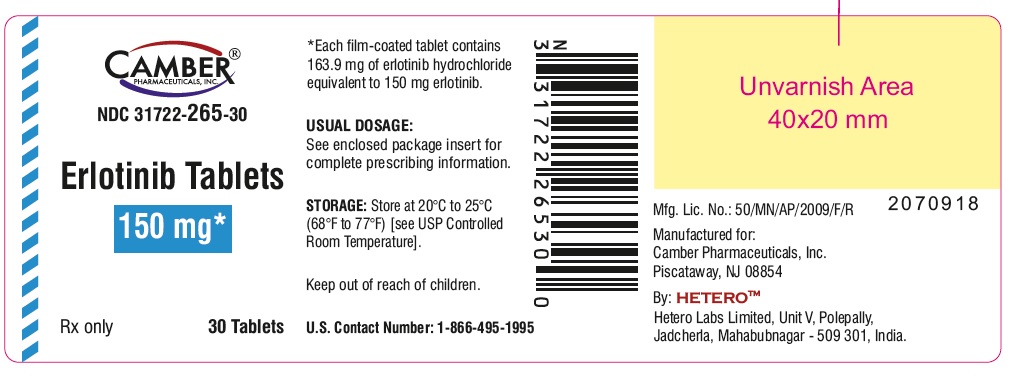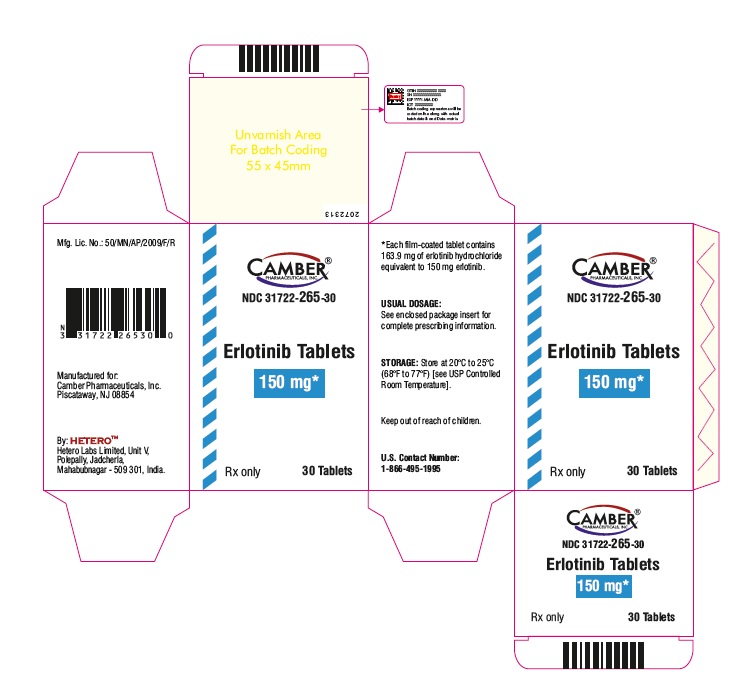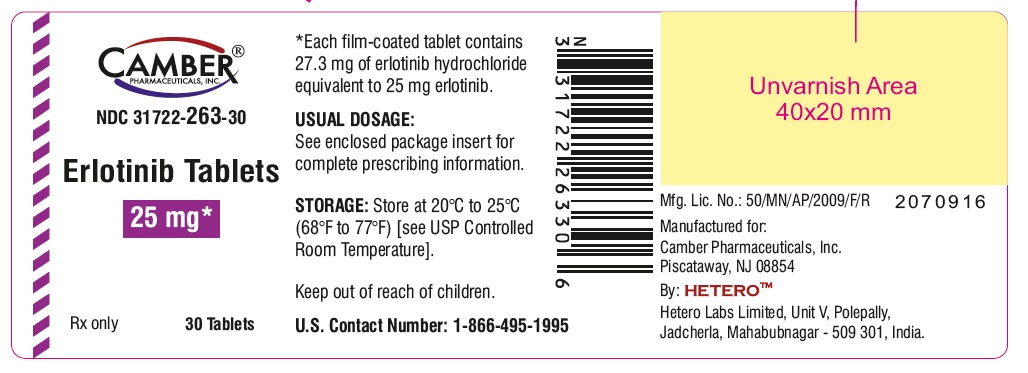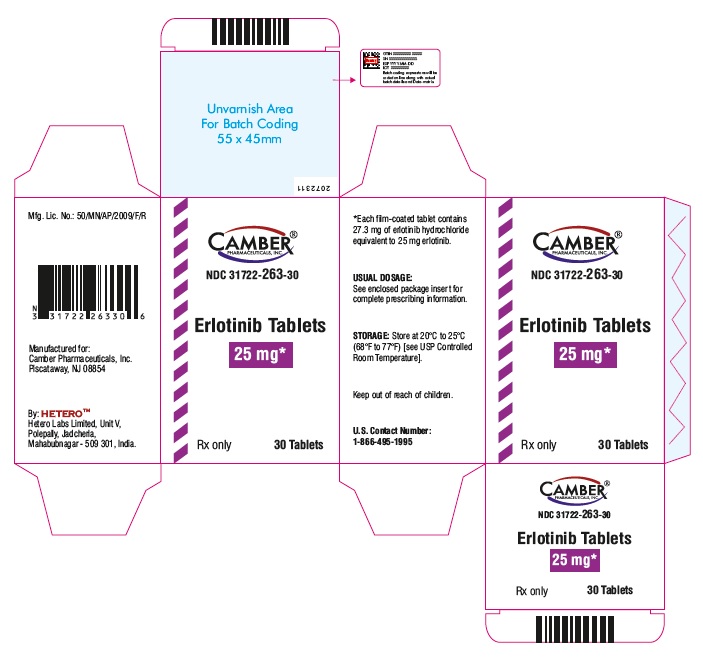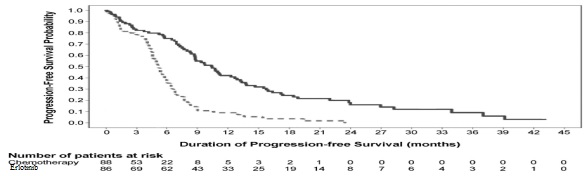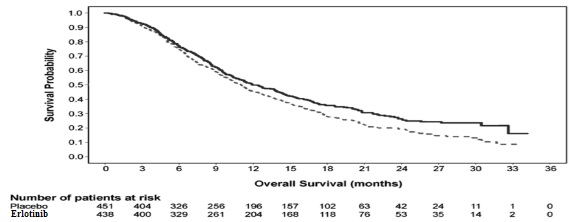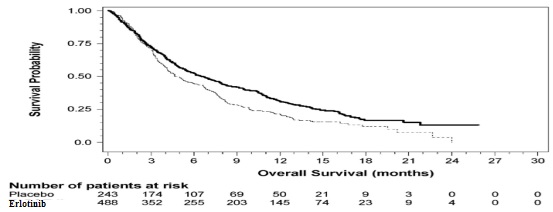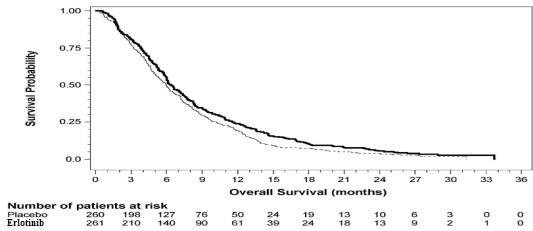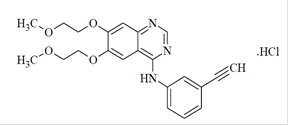 DRUG LABEL: ERLOTINIB

NDC: 31722-263 | Form: TABLET, FILM COATED
Manufacturer: Camber Pharmaceuticals, Inc.
Category: prescription | Type: HUMAN PRESCRIPTION DRUG LABEL
Date: 20240626

ACTIVE INGREDIENTS: ERLOTINIB HYDROCHLORIDE 25 mg/1 1
INACTIVE INGREDIENTS: HYDROXYPROPYL CELLULOSE, UNSPECIFIED; HYPROMELLOSE 2910 (6 MPA.S); LACTOSE MONOHYDRATE; MAGNESIUM STEARATE; POLYETHYLENE GLYCOL 400; SODIUM LAURYL SULFATE; SODIUM STARCH GLYCOLATE TYPE A POTATO; TITANIUM DIOXIDE; MICROCRYSTALLINE CELLULOSE 112

HIGHLIGHTS OF PRESCRIBING INFORMATION

These highlights do not include all the information needed to use ERLOTINIB TABLETS safely and effectively. See full prescribing information for ERLOTINIB TABLETS.
ERLOTINIB tablets, for oral use
Initial U.S. Approval: 2004

1 INDICATIONS AND USAGE

Erlotinib tablets are a kinase inhibitor indicated for:
• The treatment of patients with metastatic non-small cell lung cancer (NSCLC) whose tumors have epidermal growth factor receptor (EGFR) exon 19 deletions or exon 21 (L858R) substitution mutations as detected by an FDA-approved test receiving first-line, maintenance, or second or greater line treatment after progression following at least one prior chemotherapy regimen. (1.1)
• First-line treatment of patients with locally advanced, unresectable or metastatic pancreatic cancer, in combination with gemcitabine. (1.2)
Limitations of Use:
• Safety and efficacy of erlotinib tablets have not been established in patients with NSCLC whose tumors have other EGFR mutations. (1.1)
• Erlotinib tablets are not recommended for use in combination with platinum-based chemotherapy. (1.1)

2 DOSAGE AND ADMINISTRATION

• NSCLC: 150 mg orally, on an empty stomach, once daily. (2.2)
• Pancreatic cancer: 100 mg orally, on an empty stomach, once daily. (2.3)

3 DOSAGE FORMS AND STRENGTHS

Tablets: 25 mg, 100 mg, and 150 mg. (3)

4 CONTRAINDICATIONS

None.

5 WARNINGS AND PRECAUTIONS

• Interstitial lung disease (ILD):Occurs in 1.1% of patients. Withhold erlotinib for acute onset of new or progressive unexplained pulmonary symptoms, such as dyspnea, cough and fever. Discontinue erlotinib if ILD is diagnosed. (5.1)
• Renal failure:Monitor renal function and electrolytes, particularly in patients at risk of dehydration. Withhold erlotinib for severe renal toxicity. (5.2)
• Hepatotoxicity:Occurs with or without hepatic impairment, including hepatic failure and hepatorenal syndrome: Monitor periodic liver testing. Withhold or discontinue erlotinib for severe or worsening liver tests. (5.3)
• Gastrointestinal perforations: Discontinue erlotinib. (5.4)
• Bullous and exfoliative skin disorders:Discontinue erlotinib. (5.5)
• Cerebrovascular accident (CVA):The risk of CVA is increased in patients with pancreatic cancer. (5.6)
• Microangiopathic hemolytic anemia (MAHA):The risk of MAHA is increased in patients with pancreatic cancer. (5.7)
• Ocular disorders:Discontinue erlotinib for corneal perforation, ulceration or persistent severe keratitis. (5.8)
• Hemorrhage in patients taking warfarin:Regularly monitor INR in patients taking warfarin or other coumarin-derivative anticoagulants. (5.9)
• Embryo-fetal toxicity:Can cause fetal harm. Advise females of reproductive potential of the potential risk to the fetus and to use effective contraception. (5.10, 8.1, 8.3)

6 ADVERSE REACTIONS

The most common adverse reactions (≥ 20%) with erlotinib from a pooled analysis in patients with NSCLC across all approved lines of therapy, with and without EGFR mutations, and in patients with pancreatic cancer were rash, diarrhea, anorexia, fatigue, dyspnea, cough, nausea, and vomiting. (6.1)

To report SUSPECTED ADVERSE REACTIONS, contact Hetero Labs Limited at 1-866-495-1995 or FDA at 1-800-FDA-1088 or http://www.fda.gov/medwatch

7 DRUG INTERACTIONS

• CYP3A4 inhibitors or a combined CYP3A4 and CYP1A2 inhibitor increase erlotinib plasma concentrations. Avoid concomitant use. If not possible, reduce erlotinib dose. (2.4, 7)
• CYP3A4 inducers decrease erlotinib plasma concentrations. Avoid concomitant use. If not possible, increase erlotinib dose. (2.4, 7)
• Cigarette smoking and CYP1A2 inducers decrease erlotinib plasma concentrations. Avoid concomitant use. If not possible, increase erlotinib dose. (2.4, 7)
• Drugs that increase gastric pH decrease erlotinib plasma concentrations. For proton pump inhibitors avoid concomitant use if possible. For H-2 receptor antagonists, take erlotinib 10 hours after H-2 receptor antagonist dosing. For use with antacids, separate dosing by several hours. (2.4, 7)

8 USE IN SPECIFIC POPULATIONS

Lactation: Do not breastfeed (8.2)

FULL PRESCRIBING INFORMATION

1 INDICATIONS AND USAGE

1.1 Non-Small Cell Lung Cancer (NSCLC)

Erlotinib tablets are indicated for:
• The treatment of patients with metastatic non-small cell lung cancer (NSCLC) whose tumors have epidermal growth factor receptor (EGFR) exon 19 deletions or exon 21 (L858R) substitution mutations as detected by an FDA-approved test receiving first-line, maintenance, or second or greater line treatment after progression following at least one prior chemotherapy regimen [see Clinical Studies (14.1, 14.3)] .
Limitations of use:
• Safety and efficacy of erlotinib tablets have not been established in patients with NSCLC whose tumors have other EGFR mutations [see Clinical Studies (14.1, 14.2)] .
• Erlotinib tablets are not recommended for use in combination with platinum-based chemotherapy [see Clinical Studies (14.4)] .

1.2 Pancreatic Cancer

Erlotinib tablet in combination with gemcitabine is indicated for the first-line treatment of patients with locally advanced, unresectable or metastatic pancreatic cancer [see Clinical Studies (14.5)] .

2 DOSAGE AND ADMINISTRATION

2.1 Selection of Patients with Metastatic NSCLC

Select patients for the treatment of metastatic NSCLC with erlotinib tablets based on the presence of EGFR exon 19 deletions or exon 21 (L858R) substitution mutations in tumor or plasma specimens [See Clinical Studies (14.1, 14.2)] . If these mutations are not detected in a plasma specimen, test tumor tissue if available. Information on FDA-approved tests for the detection of EGFR mutations in NSCLC is available at: http://www.fda.gov/CompanionDiagnostics.

2.2 Recommended Dose – NSCLC

The recommended daily dose of erlotinib tablets for NSCLC is 150 mg taken on an empty stomach, i.e., at least one hour before or two hours after the ingestion of food. Treatment should continue until disease progression or unacceptable toxicity occurs.

2.3 Recommended Dose – Pancreatic Cancer

The recommended daily dose of erlotinib tablets for pancreatic cancer is 100 mg taken once daily in combination with gemcitabine. Take erlotinib tablets on an empty stomach, i.e., at least one hour before or two hours after the ingestion of food. Treatment should continue until disease progression or unacceptable toxicity occurs [see Clinical Studies (14.5)].

2.4 Dose Modifications

Adverse Reactions
Pulmonary† | Interstitial Lung Disease (ILD) | Discontinue erlotinib tablets
Pulmonary† | During diagnostic evaluation for possible ILD | Withhold erlotinib tablets*
Hepatic† | Severe hepatic toxicity that does not improve significantly or resolve within three weeks | Discontinue erlotinib tablets
Hepatic† | In patients with pre-existing hepatic impairment or biliary obstruction for doubling of bilirubin or tripling of transaminases values over baseline | Withhold erlotinib tablets*and consider discontinuation
Hepatic† | In patients without pre-existing hepatic impairment for total bilirubin levels greater than 3 times the upper limit of normal or transaminases greater than 5 times the upper limit of normal | Withhold erlotinib tablets*and consider discontinuation
Renal† | For severe (CTCAE grade 3 to 4) renal toxicity | Withhold erlotinib tablets*and consider discontinuation
Gastrointestinal† | Gastrointestinal perforation | Discontinue erlotinib tablets
Gastrointestinal† | For persistent severe diarrhea not responsive to medical management (e.g., loperamide) | Withhold erlotinib tablets*
Skin† | Severe bullous, blistering or exfoliating skin conditions | Discontinue erlotinib tablets
Skin† | For severe rash not responsive to medical management | Withhold erlotinib tablets*
Ocular† | Corneal perforation or severe ulceration | Discontinue erlotinib tablets
Ocular† | For keratitis of (NCI-CTC version 4.0) grade 3-4 or for grade 2 lasting more than 2 weeks | Withhold erlotinib tablets*
Ocular† | For acute/worsening ocular disorders such as eye pain | Withhold erlotinib tablets*and consider discontinuation
Drug Interactions
CYP3A4 inhibitors‡ | If severe reactions occur with concomitant use of strong CYP3A4 inhibitors [such as atazanavir, clarithromycin, indinavir, itraconazole, ketoconazole, nefazodone, nelfinavir, ritonavir, saquinavir, telithromycin, troleandomycin (TAO), voriconazole, or grapefruit or grapefruit juice] or when using concomitantly with an inhibitor of both CYP3A4 and CYP1A2 (e.g., ciprofloxacin) | Reduce erlotinib tablets by 50 mg decrements; avoid concomitant use if possible
CYP3A4 inducers‡ | Concomitant use with CYP3A4 inducers, such as rifampin, rifabutin, rifapentine, phenytoin, carbamazepine, phenobarbital, or St. John’s Wort | Increase erlotinib tablets by 50 mg increments at 2-week intervals to a maximum of 450 mg as tolerated. Avoid concomitant use if possible
Concurrent Cigarette Smoking‡§ | Concurrent cigarette smoking | Increase erlotinib tablets by 50 mg increments at 2-week intervals to a maximum of 300 mg. Immediately reduce the dose of erlotinib tablets to the recommended dose (150 mg or 100 mg daily) upon cessation of smoking
Proton Pump inhibitors | Separation of doses may not eliminate the interaction since proton pump inhibitors affect the pH of the upper GI tract for an extended period | Avoid concomitant use if possible
H2-receptor antagonists | If treatment with an H2-receptor antagonist such as ranitidine is required, separate dosing. | Erlotinib tablets must be taken 10 hours after the H2-receptor antagonist dosing and at least 2 hours before the next dose of the H2receptor antagonist
Antacids | The effect of antacids on erlotinib pharmacokinetics has not been evaluated. | The antacid dose and the erlotinib tablets dose should be separated by several hours, if an antacid is necessary

†For additional information see Warnings and Precautions (5).
*Reduce erlotinib by 50 mg decrements when restarting therapy following withholding treatment for a dose-limiting toxicity that has resolved to baseline or grade ≤ 1.
‡For additional information see Drug Interactions (7).
§For additional information see Clinical Pharmacology (12.3).

3 DOSAGE FORMS AND STRENGTHS

25 mg tablets
White colored, round biconvex film-coated tablets debossed with “H” on one side and “28” on the other side.
100 mg tablets
White colored, round biconvex film-coated tablets debossed with “H” on one side and “21” on the other side.
150 mg tablets
White colored, round biconvex film-coated tablets debossed with “H” on one side and “22” on the other side.

4 CONTRAINDICATIONS

None.

5 WARNINGS AND PRECAUTIONS

5.1 Interstitial Lung Disease (ILD)

Cases of serious ILD, including fatal cases, can occur with erlotinib treatment. The overall incidence of ILD in approximately 32,000 erlotinib-treated patients in uncontrolled studies and studies with concurrent chemotherapy was approximately 1.1%. In patients with ILD, the onset of symptoms was between 5 days to more than 9 months (median 39 days) after initiating erlotinib therapy.
Withhold erlotinib for acute onset of new or progressive unexplained pulmonary symptoms such as dyspnea, cough, and fever pending diagnostic evaluation. If ILD is confirmed, permanently discontinue erlotinib [see Dosage and Administration (2.4)].

5.2 Renal Failure

Hepatorenal syndrome, severe acute renal failure including fatal cases, and renal insufficiency can occur with erlotinib treatment. Renal failure may arise from exacerbation of underlying baseline hepatic impairment or severe dehydration. The pooled incidence of severe renal impairment in the 3 monotherapy lung cancer studies was 0.5% in the erlotinib arms and 0.8% in the control arms. The incidence of renal impairment in the pancreatic cancer study was 1.4% in the erlotinib plus gemcitabine arm and 0.4% in the control arm. Withhold erlotinib in patients developing severe renal impairment until renal toxicity is resolved. Perform periodic monitoring of renal function and serum electrolytes during erlotinib treatment [see Adverse Reactions (6.1) and Dosage and Administration (2.4)].

5.3 Hepatotoxicity with or without Hepatic Impairment

Hepatic failure and hepatorenal syndrome, including fatal cases, can occur with erlotinib treatment in patients with normal hepatic function; the risk of hepatic toxicity is increased in patients with baseline hepatic impairment. In clinical studies where patients with moderate to severe hepatic impairment were excluded, the pooled incidence of hepatic failure in the 3 monotherapy lung cancer studies was 0.4% in the erlotinib arms and 0% in the control arms. The incidence of hepatic failure in the pancreatic cancer study was 0.4% in the erlotinib plus gemcitabine arm and 0.4% in the control arm. In a pharmacokinetic study in 15 patients with moderate hepatic impairment (Child-Pugh B) associated with significant liver tumor burden, 10 of these 15 patients died within 30 days of the last erlotinib dose. One patient died from hepatorenal syndrome, 1 patient died from rapidly progressing liver failure and the remaining 8 patients died from progressive disease. Six out of the 10 patients who died had baseline total bilirubin > 3 x ULN.
Perform periodic liver testing (transaminases, bilirubin, and alkaline phosphatase) during treatment with erlotinib. Increased frequency of monitoring of liver function is required for patients with pre-existing hepatic impairment or biliary obstruction. Withhold erlotinib in patients without pre-existing hepatic impairment for total bilirubin levels greater than 3 times the upper limit of normal or transaminases greater than 5 times the upper limit of normal. Withhold erlotinib in patients with pre-existing hepatic impairment or biliary obstruction for doubling of bilirubin or tripling of transaminases values over baseline. Discontinue erlotinib in patients whose abnormal liver tests meeting the above criteria do not improve significantly or resolve within three weeks [see Dosage and Administration (2.4) and Clinical Pharmacology (12.3)].

5.4 Gastrointestinal Perforation

Gastrointestinal perforation, including fatal cases, can occur with erlotinib treatment. Patients receiving concomitant anti-angiogenic agents, corticosteroids, NSAIDs, or taxane-based chemotherapy, or who have prior history of peptic ulceration or diverticular disease may be at increased risk of perforation [see Adverse Reactions (6.1, 6.2)]. The pooled incidence of gastrointestinal perforation in the 3 monotherapy lung cancer studies was 0.2% in the erlotinib arms and 0.1% in the control arms. The incidence of gastrointestinal perforation in the pancreatic cancer study was 0.4% in the erlotinib plus gemcitabine arm and 0% in the control arm. Permanently discontinue erlotinib in patients who develop gastrointestinal perforation [see Dosage and Administration (2.4)].

5.5 Bullous and Exfoliative Skin Disorders

Bullous, blistering and exfoliative skin conditions, including cases suggestive of Stevens-Johnson syndrome/toxic epidermal necrolysis, which in some cases were fatal, can occur with erlotinib treatment [see Adverse Reactions (6.1, 6.2)]. The pooled incidence of bullous and exfoliative skin disorders in the 3 monotherapy lung cancer studies was 1.2% in the erlotinib arms and 0% in the control arms. The incidence of bullous and exfoliative skin disorders in the pancreatic cancer study was 0.4% in the erlotinib plus gemcitabine arm and 0% in the control arm. Discontinue erlotinib treatment if the patient develops severe bullous, blistering or exfoliating conditions [see Dosage and Administration (2.4)].

5.6 Cerebrovascular Accident

In the pancreatic carcinoma trial, seven patients in the erlotinib/gemcitabine group developed cerebrovascular accidents (incidence: 2.5%). One of these was hemorrhagic and was the only fatal event. In comparison, in the placebo/gemcitabine group there were no cerebrovascular accidents. The pooled incidence of cerebrovascular accident in the 3 monotherapy lung cancer studies was 0.6% in the erlotinib arms and not higher than that observed in the control arms.

5.7 Microangiopathic Hemolytic Anemia with Thrombocytopenia

The pooled incidence of microangiopathic hemolytic anemia with thrombocytopenia in the 3 monotherapy lung cancer studies was 0% in the erlotinib arms and 0.1% in the control arms. The incidence of microangiopathic hemolytic anemia with thrombocytopenia in the pancreatic cancer study was 1.4% in the erlotinib plus gemcitabine arm and 0% in the control arm.

5.8 Ocular Disorders

Decreased tear production, abnormal eyelash growth, keratoconjunctivitis sicca or keratitis can occur with erlotinib treatment and can lead to corneal perforation or ulceration [see A dverse Reactions (6.1)and (6.2)] . The pooled incidence of ocular disorders in the 3 monotherapy lung cancer studies was 17.8% in the erlotinib arms and 4% in the control arms. The incidence of ocular disorders in the pancreatic cancer study was 12.8% in the erlotinib plus gemcitabine arm and 11.4% in the control arm. Interrupt or discontinue erlotinib therapy if patients present with acute or worsening ocular disorders such as eye pain [see Dosage and Administration (2.4)].

5.9 Hemorrhage in Patients Taking Warfarin

Severe and fatal hemorrhage associated with International Normalized Ratio (INR) elevations can occur when erlotinib and warfarin are administered concurrently. Regularly monitor prothrombin time and INR during erlotinib treatment in patients taking warfarin or other coumarin-derivative anticoagulants [see Adverse Reactions (6.1) and Drug Interactions (7)].

5.10 Embryo-Fetal Toxicity

Based on animal data and its mechanism of action, erlotinib tablets can cause fetal harm when administered to a pregnant woman. When given during organogenesis, erlotinib administration resulted in embryo-fetal lethality and abortion in rabbits at exposures approximately 3 times the exposure at the recommended human daily dose of 150 mg. Advise pregnant women of the potential risk to a fetus.
Advise females of reproductive potential to use effective contraception during therapy and for one month after the last dose of erlotinib tablets [see Use in Specific Populations (8.1) and (8.3), Clinical Pharmacology (12.1)].

6 ADVERSE REACTIONS

The following serious adverse reactions, which may include fatalities, are discussed in greater detail in other sections of the labeling:
• Interstitial Lung Disease (ILD) [see Warnings and Precautions (5.1)]
• Renal Failure [see Warnings and Precautions (5.2)]
• Hepatotoxicity with or without Hepatic Impairment [see Warnings and Precautions (5.3)]
• Gastrointestinal Perforation [see Warnings and Precautions (5.4)]
• Bullous and Exfoliative Skin Disorders [see Warnings and Precautions (5.5)]
• Cerebrovascular Accident [see Warnings and Precautions (5.6)]
• Microangiopathic Hemolytic Anemia with Thrombocytopenia [see Warnings and Precautions (5.7)]
• Ocular Disorders [see Warnings and Precautions (5.8)]
• Hemorrhage in Patients Taking Warfarin [see Warnings and Precautions (5.9)]

6.1 Clinical Trial Experience

Because clinical trials are conducted under widely varying conditions, adverse reaction rates observed in the clinical trials of a drug cannot be directly compared to rates in the clinical trials of another drug and may not reflect the rates observed in practice.
Safety evaluation of erlotinib is based on more than 1200 cancer patients who received erlotinib as monotherapy, more than 300 patients who received erlotinib 100 or 150 mg plus gemcitabine, and 1228 patients who received erlotinib concurrently with other chemotherapies. The most common adverse reactions with erlotinib are rash and diarrhea usually with onset during the first month of treatment. The incidences of rash and diarrhea from clinical studies of erlotinib for the treatment of NSCLC and pancreatic cancer were 70% for rash and 42% for diarrhea.
Non-Small Cell Lung Cancer
First-Line Treatment of Patients with EGFR Mutations
The most frequent (≥ 30%) adverse reactions in erlotinib-treated patients were diarrhea, asthenia, rash, cough, dyspnea, and decreased appetite. In erlotinib-treated patients the median time to onset of rash was 15 days and the median time to onset of diarrhea was 32 days.
The most frequent Grade 3 to 4 adverse reactions in erlotinib-treated patients were rash and diarrhea.
Dose interruptions or reductions due to adverse reactions occurred in 37% of erlotinib-treated patients, and 14.3% of erlotinib-treated patients discontinued therapy due to adverse reactions. In erlotinib-treated patients, the most frequently reported adverse reactions leading to dose modification were rash (13%), diarrhea (10%), and asthenia (3.6%).
Common adverse reactions in Study 1, occurring in at least 10% of patients who received erlotinib or chemotherapy and an increase in ≥ 5% in the erlotinib-treated group, are graded by National Cancer Institute Common Toxicity Criteria for Adverse Events version 3.0 (NCI-CTCAE v3.0) Grade in Table 1. The median duration of erlotinib treatment was 9.6 months in Study 1.
Table 1: Adverse Reactions with an Incidence Rate ≥ 10% and an Increase of ≥ 5% in the Erlotinib-Treated Group (Study 1)

 | Erlotinib N = 84 |  | Chemotherapy† N = 83
Adverse Reaction | All Grades % | Grades 3 to 4 % | All Grades % | Grades 3 to 4 %
Rash‡ | 85 | 14 | 5 | 0
Diarrhea | 62 | 5 | 21 | 1
Cough | 48 | 1 | 40 | 0
Dyspnea | 45 | 8 | 30 | 4
Dry skin | 21 | 1 | 2 | 0
Back pain | 19 | 2 | 5 | 0
Chest pain | 18 | 1 | 12 | 0
Conjunctivitis | 18 | 0 | 0 | 0
Mucosal inflammation | 18 | 1 | 6 | 0
Pruritus | 16 | 0 | 1 | 0
Paronychia | 14 | 0 | 0 | 0
Arthralgia | 13 | 1 | 6 | 1
Musculoskeletal pain | 11 | 1 | 1 | 0

†Platinum-based chemotherapy (cisplatin or carboplatin with gemcitabine or docetaxel).
‡Rash as a composite term includes rash, acne, folliculitis, erythema, acneiform dermatitis, dermatitis, palmar-plantar erythrodysesthesia syndrome, exfoliative rash, erythematous rash, rash pruritic, skin toxicity, eczema, follicular rash, skin ulcer.
Hepatic Toxicity: One erlotinib-treated patient experienced fatal hepatic failure and four additional patients experienced grade 3 to 4 liver test abnormalities in Study 1 [see Warnings and Precautions (5.3)] .
Maintenance Treatment
Adverse reactions, regardless of causality, that occurred in at least 3% of patients treated with single-agent erlotinib at 150 mg and at least 3% more often than in the placebo group in the randomized maintenance trial (Study 3) are summarized by NCI-CTCAE v3.0 Grade in Table 2.
The most common adverse reactions in patients receiving single-agent erlotinib 150 mg were rash and diarrhea. Grade 3 to 4 rash and diarrhea occurred in 9% and 2%, respectively, in erlotinib-treated patients. Rash and diarrhea resulted in study discontinuation in 1% and 0.5% of erlotinib-treated patients, respectively. Dose reduction or interruption for rash and diarrhea was needed in 5% and 3% of patients, respectively. In erlotinib-treated patients the median time to onset of rash was 10 days, and the median time to onset of diarrhea was 15 days.
Table 2: NSCLC Maintenance Study: Adverse Reactions Occurring with an Incidence Rate ≥ 10% and an Increase of ≥ 5% in the Single-Agent Erlotinib Group compared to the Placebo Group (Study 3)

Adverse Reaction | ERLOTINIB N = 433 |  |  | PLACEBO N = 445
Adverse Reaction | Any Grade | Grade 3 | Grade 4 | Any Grade | Grade 3 | Grade 4
Adverse Reaction | % | % | % | % | % | %
Rash† | 60 | 9 | 0 | 9 | 0 | 0
Diarrhea | 20 | 2 | 0 | 4 | 0 | 0

†Rash as a composite term includes: rash, acne, acneiform dermatitis, skin fissures, erythema, papular rash, rash generalized, pruritic rash, skin exfoliation, urticaria, dermatitis, eczema, exfoliative rash, exfoliative dermatitis, furuncle, macular rash, pustular rash, skin hyperpigmentation, skin reaction, skin ulcer.

Liver test abnormalities including ALT elevations were observed at Grade 2 or greater severity in 3% of erlotinib-treated patients and 1% of placebo-treated patients. Grade 2 and above bilirubin elevations were observed in 5% of erlotinib-treated patients and in < 1% in the placebo group [see Dosage and Administration (2.4) and Warnings and Precautions (5.3)].
Second/Third Line Treatment
Adverse reactions, regardless of causality, that occurred in at least 10% of patients treated with single-agent erlotinib at 150 mg and at least 5% more often than in the placebo group in the randomized trial of patients with NSCLC are summarized by NCI-CTC v2.0 Grade in Table 3.
The most common adverse reactions in this patient population were rash and diarrhea. Grade 3 to 4 rash and diarrhea occurred in 9% and 6%, respectively, in erlotinib-treated patients. Rash and diarrhea each resulted in study discontinuation in 1% of erlotinib-treated patients. Six percent and 1% of patients needed dose reduction for rash and diarrhea, respectively. The median time to onset of rash was 8 days, and the median time to onset of diarrhea was 12 days.
Table 3: NSCLC 2nd/3rdLine Study: Adverse Reactions Occurring with an Incidence Rate ≥ 10% and an Increase of ≥ 5% in the Single-Agent Erlotinib Group Compared to the Placebo Group (Study 4)

Adverse Reaction | Erlotinib 150 mg N=485 |  |  | Placebo N=242
Adverse Reaction | Any Grade | Grade 3 | Grade 4 | Any Grade | Grade 3 | Grade 4
Adverse Reaction | % | % | % | % | % | %
Rash† | 75 | 8 | <1 | 17 | 0 | 0
Diarrhea | 54 | 6 | <1 | 18 | <1 | 0
Anorexia | 52 | 8 | 1 | 38 | 5 | <1
Fatigue | 52 | 14 | 4 | 45 | 16 | 4
Dyspnea | 41 | 17 | 11 | 35 | 15 | 11
Nausea | 33 | 3 | 0 | 24 | 2 | 0
Infection | 24 | 4 | 0 | 15 | 2 | 0
Stomatitis | 17 | <1 | 0 | 3 | 0 | 0
Pruritus | 13 | <1 | 0 | 5 | 0 | 0
Dry skin | 12 | 0 | 0 | 4 | 0 | 0
Conjunctivitis | 12 | <1 | 0 | 2 | <1 | 0
Keratoconjunctivitis sicca | 12 | 0 | 0 | 3 | 0 | 0

†Rash as a composite term includes: rash, palmar-plantar erythrodysesthesia syndrome, acne, skin disorder, pigmentation disorder, erythema, skin ulcer, exfoliative dermatitis, papular rash, skin desquamation.
Liver function test abnormalities [including elevated alanine aminotransferase (ALT), aspartate aminotransferase (AST) and bilirubin] were observed in patients receiving single-agent erlotinib 150 mg. These elevations were mainly transient or associated with liver metastases. Grade 2 [>2.5 to 5.0 x upper limit of normal (ULN)] ALT elevations occurred in 4% and < 1% of erlotinib and placebo treated patients, respectively. Grade 3 (>5.0 to 20.0 x ULN) elevations were not observed in erlotinib-treated patients. Erlotinib dosing should be interrupted or discontinued if changes in liver function are severe [see Dosage and Administration (2.4)].
Pancreatic Cancer - Erlotinib Administered Concurrently with Gemcitabine
This was a randomized, double-blind, placebo-controlled study of erlotinib (150 mg or 100 mg daily) or placebo plus gemcitabine (1000 mg/m^2by intravenous infusion) in patients with locally advanced, unresectable or metastatic pancreatic cancer (Study 5). The safety population comprised 282 patients in the erlotinib group (259 in the 100 mg cohort and 23 in the 150 mg cohort) and 280 patients in the placebo group (256 in the 100 mg cohort and 24 in the 150 mg cohort).
Adverse reactions that occurred in at least 10% of patients treated with erlotinib 100 mg plus gemcitabine in the randomized trial of patients with pancreatic cancer (Study 5) were graded according to NCI-CTC v2.0 in Table 4.
The most common adverse reactions in pancreatic cancer patients receiving erlotinib 100 mg plus gemcitabine were fatigue, rash, nausea, anorexia and diarrhea. In the erlotinib plus gemcitabine arm, Grade 3 to 4 rash and diarrhea were each reported in 5% of patients. The median time to onset of rash and diarrhea was 10 days and 15 days, respectively. Rash and diarrhea each resulted in dose reductions in 2% of patients, and resulted in study discontinuation in up to 1% of patients receiving erlotinib plus gemcitabine. Severe adverse reactions (≥ Grade 3 NCI-CTC) in the erlotinib plus gemcitabine group with incidences < 5% included syncope, arrhythmias, ileus, pancreatitis, hemolytic anemia including microangiopathic hemolytic anemia with thrombocytopenia, myocardial infarction/ischemia, cerebrovascular accidents including cerebral hemorrhage, and renal insufficiency [see Warnings and Precautions (5)].
The 150 mg cohort was associated with a higher rate of certain class-specific adverse reactions including rash and required more frequent dose reduction or interruption.
Table 4: Adverse Reactions Occurring with an Incidence Rate ≥ 10% and an Increase of ≥ 5% in Erlotinib-Treated Pancreatic Cancer Patients: 100 mg Cohort (Study 5)

Adverse Reaction | Erlotinib+ Gemcitabine 1000 mg/m^2IV N=259 |  |  | Placebo + Gemcitabine 1000 mg/m^2IV N=256
Adverse Reaction | Any Grade | Grade 3 | Grade 4 | Any Grade | Grade 3 | Grade 4
Adverse Reaction | % | % | % | % | % | %
Rash† | 70 | 5 | 0 | 30 | 1 | 0
Diarrhea | 48 | 5 | <1 | 36 | 2 | 0
Decreased weight | 39 | 2 | 0 | 29 | <1 | 0
Infection* | 39 | 13 | 3 | 30 | 9 | 2
Pyrexia | 36 | 3 | 0 | 30 | 4 | 0
Stomatitis | 22 | <1 | 0 | 12 | 0 | 0
Depression | 19 | 2 | 0 | 14 | <1 | 0
Cough | 16 | 0 | 0 | 11 | 0 | 0
Headache | 15 | <1 | 0 | 10 | 0 | 0

*Infections as a composite term include infections with unspecified pathogens as well as bacterial (including chlamydial, rickettsial, mycobacterial and mycoplasmal), parasitic (including helminthic, ectoparasitic and protozoal), viral and fungal infectious disorders.
†Rash as a composite term includes: rash, palmar-plantar erythrodysesthesia syndrome, pigmentation disorder, acneiform dermatitis, folliculitis, photosensitivity reaction, Stevens-Johnson syndrome, urticaria, erythematous rash, skin disorder, skin ulcer.
Ten patients (4%) in the erlotinib/gemcitabine group and three patients (1%) in the placebo/gemcitabine group developed deep venous thrombosis. The overall incidence of grade 3 or 4 thrombotic events, including deep venous thrombosis was 11% for erlotinib plus gemcitabine and 9% for placebo plus gemcitabine.
The incidences of liver test abnormalities (≥ Grade 2) in Study 5 are provided in Table 5 [see Dosage and Administration (2.4) and Warnings and Precautions (5.3)].
Table 5: Liver Test Abnormalities in Pancreatic Cancer Patients: 100 mg Cohort (Study 5)

 | Erlotinib+ Gemcitabine 1000 mg/m^2IV N=259 |  |  | Placebo + Gemcitabine 1000 mg/m^2IV N=256
 | Grade 2 | Grade 3 | Grade 4 | Grade 2 | Grade 3 | Grade 4
Bilirubin | 17% | 10% | <1% | 11% | 10% | 3%
ALT | 31% | 13% | <1% | 22% | 9% | 0%
AST | 24% | 10% | <1% | 19% | 9% | 0%

NSCLC and Pancreatic Indications: Selected Low Frequency Adverse Reactions
Gastrointestinal Disorders
Cases of gastrointestinal bleeding (including fatalities) have been reported, some associated with concomitant warfarin or NSAID administration [see Warnings and Precautions (5.9) and Drug Interactions (7)]. These adverse reactions were reported as peptic ulcer bleeding (gastritis, gastroduodenal ulcers), hematemesis, hematochezia, melena and hemorrhage from possible colitis.

6.2 Post-Marketing Experience

The following adverse reactions have been identified during post approval use of erlotinib. Because these reactions are reported voluntarily from a population of uncertain size, it is not always possible to reliably estimate their frequency or establish a causal relationship to drug exposure.
Musculoskeletal and Connective Tissue Disorders:myopathy, including rhabdomyolysis, in combination with statin therapy
Eye Disorders: ocular inflammation including uveitis

7 DRUG INTERACTIONS

CYP3A4 Inhibitors
Co-administration of erlotinib with a strong CYP3A4 inhibitor or a combined CYP3A4 and CYP1A2 inhibitor increased erlotinib exposure. Erlotinib is metabolized primarily by CYP3A4 and to a lesser extent by CYP1A2. Increased erlotinib exposure may increase the risk of exposure-related toxicity [see Clinical Pharmacology (12.3)].
Avoid co-administering erlotinib with strong CYP3A4 inhibitors (e.g., boceprevir, clarithromycin, conivaptan, indinavir, itraconazole, ketoconazole, lopinavir/ritonavir, nefazodone, nelfinavir, posaconazole, ritonavir, saquinavir, telithromycin, voriconazole, grapefruit or grapefruit juice) or a combined CYP3A4 and CYP1A2 inhibitor (e.g., ciprofloxacin). Reduce the erlotinib dosage when co-administering with a strong CYP3A4 inhibitor or a combined CYP3A4 and CYP1A2 inhibitor if co-administration is unavoidable [see Dosage and Administration (2.4)].
CYP3A4 Inducers
Pre-treatment with a CYP3A4 inducer prior to erlotinib decreased erlotinib exposure [see Clinical Pharmacology (12.3)]. Increase the erlotinib dosage if co-administration with CYP3A4 inducers (e.g., carbamazepine, phenytoin, rifampin, rifabutin, rifapentine, phenobarbital and St. John's wort) is unavoidable [see Dosage and Administration (2.4)].
CYP1A2 Inducers and Cigarette Smoking
Cigarette smoking decreased erlotinib exposure. Avoid smoking tobacco (CYP1A2 inducer) and avoid concomitant use of erlotinib with moderate CYP1A2 inducers (e.g., teriflunomide, rifampin, or phenytoin). Increase the erlotinib dosage in patients that smoke tobacco or when co-administration with moderate CYP1A2 inducers is unavoidable [see Dosage and Administration (2.4) and Clinical Pharmacology (12.3)].
Drugs the Increase Gastric pH
Co-administration of erlotinib with proton pump inhibitors (e.g., omeprazole) and H-2 receptor antagonists (e.g., ranitidine) decreased erlotinib exposure [see Clinical Pharmacology (12.3)]. For proton pump inhibitors, avoid concomitant use if possible. For H-2 receptor antagonists and antacids, modify the dosing schedule [see Dosage and Administration (2.4)]. Increasing the dose of erlotinib when co-administered with gastric pH elevating agents is not likely to compensate for the loss of exposure.
Anticoagulants
Interaction with coumarin-derived anticoagulants, including warfarin, leading to increased International Normalized Ratio (INR) and bleeding adverse reactions, which in some cases were fatal, have been reported in patients receiving erlotinib. Regularly monitor prothrombin time or INR in patients taking coumarin-derived anticoagulants. Dose modifications of erlotinib are not recommended [see Warnings and Precautions (5.9) and Adverse Reactions (6.1)].

8 USE IN SPECIFIC POPULATIONS

8.1 Pregnancy

Risk Summary
Based on animal data and its mechanism of action, erlotinib can cause fetal harm when administered to a pregnant woman. Limited available data on use of erlotinib in pregnant women are not sufficient to inform a risk of major birth defects or miscarriage. When given during organogenesis, erlotinib administration resulted in embryo-fetal lethality and abortion in rabbits at exposures approximately 3 times the exposure at the recommended human daily dose of 150 mg. Advise pregnant women of the potential risk to a fetus.
In the U.S. general population, the estimated background risk of major birth defects and miscarriage in clinically recognized pregnancies is 2 to 4% and 15 to 20%, respectively.
Data
Animal Data
Erlotinib has been shown to cause maternal toxicity resulting in embryo-fetal lethality and abortion in rabbits when given during the period of organogenesis at doses that result in plasma drug concentrations approximately 3 times those achieved at the recommended dose in humans (AUCs at 150 mg daily dose). During the same period, there was no increase in the incidence of embryo-fetal lethality or abortion in rabbits or rats at doses resulting in exposures approximately equal to those in humans at the recommended daily dose. In an independent fertility study female rats treated with 30 mg/m^2/day or 60 mg/m^2/day (0.3 or 0.7 times the recommended daily dose, on a mg/m^2basis) of erlotinib had an increase in early resorptions that resulted in a decrease in the number of live fetuses.
No teratogenic effects were observed in rabbits or rats dosed with erlotinib during organogenesis at doses up to 600 mg/m^2/day in the rabbit (3 times the plasma drug concentration seen in humans at 150 mg/day) and up to 60 mg/m^2/day in the rat (0.7 times the recommended dose of 150 mg/day on a mg/m^2basis).

8.2 Lactation

Risk Summary
There are no data on the presence of erlotinib in human milk, or the effects of erlotinib on the breastfed infant or on milk production. Because of the potential for serious adverse reactions in breastfed infants from erlotinib, including interstitial lung disease, hepatotoxicity, bullous and exfoliative skin disorders, microangiopathic hemolytic anemia with thrombocytopenia, ocular disorders, and diarrhea. Advise a lactating woman not to breastfeed during treatment with erlotinib and for 2 weeks after the final dose.

8.3 Females and Males of Reproductive Potential

Contraception
Females
Erlotinib can cause fetal harm when administered to a pregnant woman [see Use in Specific Populations (8.1)]. Advise females of reproductive potential to use effective contraception during treatment with erlotinib and for one month after the last dose of erlotinib.

8.4 Pediatric Use

The safety and effectiveness of erlotinib in pediatric patients have not been established.
In an open-label, multicenter trial, 25 pediatric patients (median age 14 years, range 3 to 20 years) with recurrent or refractory ependymoma were randomized (1:1) to erlotinib or etoposide. Thirteen patients received erlotinib at a dose of 85 mg/m^2/day orally until disease progression, death, patient request, investigator decision to discontinue study drug, or intolerable toxicity. Four patients randomized to etoposide also received erlotinib following disease progression. The trial was terminated prematurely for lack of efficacy; there were no objective responses observed in these 17 erlotinib-treated patients.
No new adverse events were identified in the pediatric population.
Based on the population pharmacokinetics analysis conducted in 105 pediatric patients (2 to 21 years old) with cancer, the geometric mean estimates of CL/F/BSA (apparent clearance normalized to body surface area) were comparable across the three age groups: 2 to 6 years (n=29), 7 to 16 years (n=59), and 17 to 21 years (n=17).

8.5 Geriatric Use

Of the 1297 subjects in clinical studies of erlotinib for the treatment of NSCLC and pancreatic cancer 40% were 65 and older while 10% were 75 and older. No overall differences in safety or efficacy were observed between subjects 65 years and older and those younger than 65.

8.6 Hepatic Impairment

Hepatic failure and hepatorenal syndrome, including fatal cases, can occur with erlotinib treatment in patients with normal hepatic function; the risk of hepatic toxicity is increased in patients with baseline hepatic impairment [see Warnings and Precautions (5.3), Adverse Reactions (6.1, 6.2), and Dosage and Administration]. Monitor patients with hepatic impairment (total bilirubin greater than upper limit of normal (ULN) or Child-Pugh A, B and C) during therapy with erlotinib. Treatment with erlotinib should be used with increased monitoring in patients with total bilirubin greater than 3 x ULN [see Warnings and Precautions (5.3), Adverse Reactions (6.1, 6.2), and Dosage and Administration (2.4)].

10 OVERDOSAGE

Withhold erlotinib in patients with an overdose or suspected overdose and institute symptomatic treatment.

11 DESCRIPTION

Erlotinib, a kinase inhibitor, is a quinazolinamine with the chemical name N-(3-Ethynylphenyl)-6,7-bis(2-methoxyethoxy)-4-quinazolinamine Hydrochloride. Erlotinib contains erlotinib as the hydrochloride salt that has the following structural formula:

Erlotinib hydrochloride has the molecular formula C22H23N3O4.HCl and a molecular weight of 429.90. The molecule has a pkaof 5.6. Erlotinib hydrochloride is a white to an off-white crystalline powder. Erlotinib hydrochloride is very slightly soluble in methanol.
Erlotinib tablets for oral administration are available in three dosage strengths containing erlotinib hydrochloride (27.3 mg, 109.3 mg and 163.9 mg) equivalent to 25 mg, 100 mg and 150 mg erlotinib and the following inactive ingredients: hydroxypropyl cellulose, hypromellose, lactose monohydrate, magnesium stearate, microcrystalline cellulose, polyethylene glycol, sodium lauryl sulfate, sodium starch glycolate and titanium dioxide.

12 CLINICAL PHARMACOLOGY

12.1 Mechanism of Action

Epidermal growth factor receptor (EGFR) is expressed on the cell surface of both normal and cancer cells. In some tumor cells signaling through this receptor plays a role in tumor cell survival and proliferation irrespective of EGFR mutation status. Erlotinib reversibly inhibits the kinase activity of EGFR, preventing autophosphorylation of tyrosine residues associated with the receptor and thereby inhibiting further downstream signaling. Erlotinib binding affinity for EGFR exon 19 deletion or exon 21 (L858R) mutations is higher than its affinity for the wild type receptor. Erlotinib inhibition of other tyrosine kinase receptors has not been fully characterized.

12.3 Pharmacokinetics

Absorption
Erlotinib is about 60% absorbed after oral administration. Peak plasma levels occur 4 hours after dosing.
Effect of Food
Food increased the bioavailability of erlotinib to approximately 100%.
Distribution:
Erlotinib is 93% protein bound to plasma albumin and alpha-1 acid glycoprotein (AAG).
Erlotinib has an apparent volume of distribution of 232 liters.
Elimination
Erlotinib is eliminated with a median half-life of 36.2 hours in patients receiving the single-agent erlotinib 2nd/3rdline regimen. Time to reach steady state plasma concentration would therefore be 7 to 8 days.
Metabolism
Erlotinib is metabolized primarily by CYP3A4 and to a lesser extent by CYP1A2, and the extrahepatic isoform CYP1A1, in vitro.
Excretion
Following a 100 mg oral dose, 91% of the dose was recovered: 83% in feces (1% of the dose as intact parent) and 8% in urine (0.3% of the dose as intact parent).
Specific Populations
Neither age, body weight, nor gender had a clinically significant effect on the systemic exposure of erlotinib in NSCLC patients receiving single-agent erlotinib for 2nd/3rdline treatment or for maintenance treatment, and in pancreatic cancer patients who received erlotinib plus gemcitabine. The pharmacokinetics of erlotinib in patients with compromised renal function is unknown.
Patients with Hepatic Impairment
In vitroand in vivoevidence suggest that erlotinib is cleared primarily by the liver. However, erlotinib exposure was similar in patients with moderately impaired hepatic function (Child-Pugh B) compared with patients with adequate hepatic function including patients with primary liver cancer or hepatic metastases.
Patients That Smoke Tobacco Cigarettes
In a single-dose pharmacokinetics trial in healthy volunteers, cigarette smoking (moderate CYP1A2 inducer) increased erlotinib clearance and decreased erlotinib AUC0 to infby 64% (95% CI, 46 to 76%) in current smokers compared with former/never smokers. In a NSCLC trial, current smokers achieved erlotinib steady-state trough plasma concentrations which were approximately 2-fold less than the former smokers or patients who had never smoked. This effect was accompanied by a 24% increase in apparent erlotinib plasma clearance. In another study which was conducted in NSCLC patients who were current smokers, pharmacokinetic analyses at steady-state indicated a dose-proportional increase in erlotinib exposure when the erlotinib dose was increased from 150 mg to 300 mg. [see Dosage and Administration (2.4), Drug Interactions (7) and Patient Counseling Information (17)].
Drug Interaction Studies
Co-administration of gemcitabine had no effect on erlotinib plasma clearance.
CYP3A4 Inhibitors
Co-administration with a strong CYP3A4 inhibitor, ketoconazole, increased erlotinib AUC by 67%. Co-administration with a combined CYP3A4 and CYP1A2 inhibitor, ciprofloxacin, increased erlotinib exposure [AUC] by 39%, and increased erlotinib maximum concentration [Cmax] by 17%. [see Dose Modifications (2.4), Drug Interactions (7)].
CYP3A4 Inducers
Pre-treatment with the CYP3A4 inducer rifampicin, for 7 to 11 days prior to erlotinib, decreased erlotinib AUC by 58% to 80% [see Dose Modifications (2.4), Drug Interactions (7)].
CYP1A2 Inducers or Smoking Tobacco
See Specific Populations Section [see Dose Modifications (2.4), Drug Interactions (7)].
Drugs that Increase Gastric pH
Erlotinib solubility is pH dependent and decreases as pH increases. When a proton pump inhibitor (omeprazole) was co-administered with erlotinib the erlotinib exposure [AUC] was decreased by 46% and the erlotinib maximum concentration [Cmax] was decreased by 61%. When erlotinib was administered 2 hours following a 300 mg dose of an H-2 receptor antagonist (ranitidine), the erlotinib AUC was reduced by 33% and the erlotinib Cmaxwas reduced by 54%. When erlotinib was administered with ranitidine 150 mg twice daily (at least 10 h after the previous ranitidine evening dose and 2 h before the ranitidine morning dose), the erlotinib AUC was decreased by 15% and the erlotinib Cmaxwas decreased by 17% [see Dose Modifications (2.4), Drug Interactions (7)].

13 NONCLINICAL TOXICOLOGY

13.1 Carcinogenesis, Mutagenesis, Impairment of Fertility

Two-year carcinogenicity studies were conducted in mice and rats with erlotinib at oral doses of up to 60 mg/kg/day in mice, 5 mg/kg/day in female rats, and 10 mg/kg/day in male rats. The studies were negative for carcinogenic findings. Exposure in mice at the highest dose tested was approximately 10 times the exposure in humans at the erlotinib dose of 150 mg/day. The highest dose evaluated in male rats resulted in exposures that were twice those in humans and exposures at the highest tested dose in female rats were slightly lower than those in humans.
Erlotinib did not cause genetic damage in a series of in vitroassays (bacterial mutation, human lymphocyte chromosome aberration and mammalian cell mutation) and in the in vivomouse bone marrow micronucleus test.
Erlotinib did not impair fertility in either male or female rats.

14 CLINICAL STUDIES

14.1 Non-Small Cell Lung Cancer (NSCLC) – First-Line Treatment of Patients with EGFR Mutations

Study 1
The safety and efficacy of erlotinib as monotherapy for the first-line treatment of patients with metastatic NSCLC containing EGFR exon 19 deletions or exon 21 (L858R) substitution mutations was demonstrated in Study 1, a randomized, open-label, clinical trial conducted in Europe. One hundred seventy-four (174) White patients were randomized 1:1 to receive erlotinib 150 mg once daily until disease progression (n = 86) or four cycles of a standard platinum-based doublet chemotherapy (n = 88); standard chemotherapy regimens were cisplatin plus gemcitabine, cisplatin plus docetaxel, carboplatin plus gemcitabine, and carboplatin plus docetaxel. The main efficacy outcome measure was progression-free survival (PFS) as assessed by the investigator. Randomization was stratified by EGFR mutation (exon 19 deletion or exon 21 (L858R) substitution) and Eastern Cooperative Oncology Group Performance Status (ECOG PS) (0 vs. 1 vs. 2). EGFR mutation status for screening and enrollment of patients was determined by a clinical trials assay (CTA). Tumor samples from 134 patients (69 patients from the erlotinib arm and 65 patients from the chemotherapy arm) were tested retrospectively by the FDA-approved companion diagnostic, cobas®EGFR Mutation Test.
Baseline demographics of the overall study population were: female (72%), White (99%), age ≥ 65 years (51%), ECOG PS 1 (53%), with ECOG PS 0 (33%), and ECOG PS 2 (14%), current smoker (11%), past-smoker (20%), and never smoker (69%). The disease characteristics were 93% Stage IV and 7% Stage IIIb with pleural effusion as classified by the American Joint Commission on Cancer (AJCC, 6thedition), 93% adenocarcinoma, 66% exon 19 mutation deletions and 34% exon 21 (L858R) point mutation by CTA.
A statistically significant improvement in investigator-determined PFS (based on RECIST 1.0 or clinical progression) was demonstrated for patients randomized to erlotinib compared to those randomized to chemotherapy (see Table 6 and Figure 1). Similar results for PFS (based on RECIST 1.0) were observed for the subgroup evaluated by an independent-review committee (approximately 75% of patients evaluated in Study 1) and in the subgroup of 134 patients (77% of Study 1 population) with EGFR mutations confirmed by the cobas®EGFR Mutation Test.
A protocol-specified analysis of overall survival (OS) conducted at the time of the final analysis of PFS showed no statistically significant difference between the erlotinib and chemotherapy arms. At the time of the data cut-off, 84% of patients in the chemotherapy arm had received at least one subsequent treatment, of whom 97% received an EGFR-tyrosine kinase inhibitor. In the erlotinib arm, 66% of patients had received at least one subsequent treatment.
Table 6: Efficacy Results (Study 1)

Efficacy Parameter | Erlotinib (N = 86) | Chemotherapy (N = 88)
Progression-Free Survival
Number of Progressions or Deaths | 71 (83%) | 63 (72%)
Median PFS in Months (95% CI) | 10.4 (8.7, 12.9) | 5.2 (4.6, 6.0)
Hazard Ratio (95% CI)(1) | 0.34 (0.23, 0.49)
p-value (unstratified log-rank test) | <0.001
Overall Survival
Number of Deaths (%) | 55 (64%) | 54 (61%)
Median OS in Months (95% CI) | 22.9 (17.0, 26.8) | 19.5 (17.3, 28.4)
Hazard Ratio (95% CI)^1 | 0.93 (0.64, 1.35)
Objective Response
Objective Response Rate (95% CI) | 65% (54.1%, 75.1%) | 16% (9.0%, 25.3%)

(1)Unstratified Cox regression model.
Figure 1: Kaplan-Meier Curves of Investigator-Assessed PFS in Study 1

In exploratory subgroup analyses based on EGFR mutation subtype, the hazard ratio (HR) for PFS was 0.27 (95% CI 0.17 to 0.43) in patients with exon 19 deletions and 0.52 (95% CI 0.29 to 0.95) in patients with exon 21 (L858R) substitution. The HR for OS was 0.94 (95% CI 0.57 to 1.54) in the exon 19 deletion subgroup and 0.99 (95% CI 0.56 to 1.76) in the exon 21 (L858R) substitution subgroup.

14.2 NSCLC - Lack of Efficacy of Erlotinib in Maintenance Treatment of Patients without EGFR Mutations

Lack of efficacy of erlotinib for the maintenance treatment of patients with NSCLC without EGFR activating mutations was demonstrated in Study 2. Study 2 was a multicenter, placebo-controlled, randomized trial of 643 patients with advanced NSCLC without an EGFR exon 19 deletion or exon 21 L858R mutation who had not experienced disease progression after four cycles of platinum-based chemotherapy. Patients were randomized 1:1 to receive erlotinib 150 mg or placebo orally once daily (322 erlotinib, 321 placebo) until disease progression or unacceptable toxicity. Following progression on initial therapy, patients were eligible to enter an open-label phase. Baseline characteristics were as follows: median age 61 years (35% age ≥ 65 years), 75% male, 77% White, 21% Asian, 28% ECOG PS 0, 72% ECOG PS 1, 16% never smokers, 58% current smokers, 57% adenocarcinoma, 35% squamous cell carcinoma, 22% stage IIIB disease not amenable to combined modality treatment, and 78% stage IV disease. Fifty percent of patients randomized to erlotinib entered the open-label phase and received chemotherapy, while 77% of patients randomized to placebo entered the open-label phase and received erlotinib.
The main efficacy outcome was overall survival (OS). Median OS was 9.7 months in the erlotinib arm and 9.5 months in the placebo arm; the hazard ratio for OS was 1.02 (95% CI 0.85, 1.22). Median PFS was 3.0 months in the erlotinib arm and 2.8 months in the placebo arm; the hazard ratio for PFS was 0.94 (95% CI 0.80, 1.11).

14.3 NSCLC - Maintenance Treatment or Second/Third Line Treatment

Two randomized, double-blind, placebo-controlled trials, Studies 3 and 4, examined the efficacy and safety of erlotinib administered to patients with metastatic NSCLC as maintenance therapy after initial treatment with chemotherapy (Study 3) or with disease progression following initial treatment with chemotherapy (Study 4). Determination of EGFR mutation status was not required for enrollment.
Study 3
The efficacy and safety of erlotinib as maintenance treatment of NSCLC were demonstrated in Study 3, a randomized, double-blind, placebo-controlled trial conducted in 26 countries, in 889 patients with metastatic NSCLC whose disease did not progress during first-line platinum-based chemotherapy. Patients were randomized 1:1 to receive erlotinib 150 mg or placebo orally once daily (438 erlotinib, 451 placebo) until disease progression or unacceptable toxicity. The primary objective of the study was to determine if the administration of erlotinib after standard platinum-based chemotherapy in the treatment of NSCLC resulted in improved progression-free survival (PFS) when compared with placebo, in all patients or in patients with EGFR immunohistochemistry (IHC) positive tumors.
Baseline demographics of the overall study population were as follows: male (74%), age < 65 years (66%), ECOG PS 1 (69%), ECOG PS 0 (31%), white (84%), Asian (15%), current smoker (55%), past-smoker (27%), and never smoker (17%). Disease characteristics were as follows: Stage IV (75%), Stage IIIb with effusion (25%) as classified by AJCC (6thedition) with histologic subtypes of adenocarcinoma including bronchioalveolar (45%), squamous (40%) and large cell (5%); and EGFR IHC positive (70%), negative (14%), indeterminate (4%), and missing (12%).
Table 7: Efficacy Results (Study 3): (ITT Population)^1

Efficacy Parameter | Erlotinib (N = 438) | Placebo (N = 451)
Progression-Free Survival (PFS) based on investigator assessment
Number of Progression or Deaths (%) | 349 (80%) | 400 (89%)
Median PFS in Months (95% CI) | 2.8 (2.8, 3.1) | 2.6 (1.9, 2.7)
Hazard Ratio (95% CI)(2) | 0.71 (0.62, 0.82)
p-value (stratified log-rank test)(2,3) | p < 0.0001
Overall Survival (OS)
Number of Deaths | 298 (68%) | 350 (78%)
Median OS in Months (95% CI) | 12.0 (10.6, 13.9) | 11.0 (9.9, 12.1)
Hazard Ratio (95% CI)(2) | 0.81 (0.70, 0.95)
p-value (stratified log-rank test)(3) | 0.0088

(1)Patients with PD prior to randomization were excluded from PFS and TTP analysis.
(2)Univariate Cox regression model.
(3)Unstratified log-rank test.
Figure 2 depicts the Kaplan-Meier Curves for Overall Survival (ITT Population).
Figure 2: Kaplan-Meier Curves for Overall Survival of Patients by Treatment Group in Study 3

Note: HR is from a univariate Cox regression model.
Study 4
The efficacy and safety of single-agent erlotinib was assessed in Study 4, a randomized, double blind, placebo-controlled trial in 731 patients with locally advanced or metastatic NSCLC after failure of at least one chemotherapy regimen. Patients were randomized 2:1 to receive erlotinib 150 mg or placebo (488 erlotinib, 243 placebo) orally once daily until disease progression or unacceptable toxicity. Efficacy outcome measures included overall survival, response rate, and progression-free survival (PFS). Duration of response was also examined. The primary endpoint was survival. The study was conducted in 17 countries.
Baseline demographics of the overall study population were as follows: male (65%), White (78%), Asian (12%), Black (4%), age < 65 years (62%), ECOG PS 1 (53%), ECOG PS 0 (13%), ECOG PS 2 (25%), ECOG PS 3 (9%), current or ex-smoker (75%), never smoker (20%), and exposure to prior platinum therapy (93%). Tumor characteristics were as follows: adenocarcinoma (50%), squamous (30%), undifferentiated large cell (9%), and mixed non-small cell (2%).
The results of the study are shown in Table 8.

Table 8: Efficacy Results (Study 4)

Efficacy Parameter | Erlotinib (N = 488) | Placebo (N = 243)
Overall Survival (OS)
Number of Deaths | 378 (77%) | 209 (86%)
Median OS in Months (95% CI) | 6.7 (5.5, 7.8) | 4.7 (4.1, 6.3)
Hazard Ratio (95% CI)(1) | 0.73 (0.61, 0.86)
p-value (stratified log-rank test)(2) | p < 0.001
Progression-Free Survival (PFS)
Number of Progression or Deaths (%) | 402 (82%) | 211 (87%)
Median PFS in Months (95% CI) | 2.3 (1.9, 3.3) | 1.8 (1.8, 1.9)
Hazard Ratio (95% CI)^1 | 0.59 (0.50, 0.70)
Objective Response
Objective Response Rate (95% CI) | 8.9% (6.4, 12.0) | 0.9% (0.1, 3.4)

(1)Cox regression model with the following covariates: ECOG performance status, number of prior regimens, prior platinum, best response to prior chemotherapy.
(2)Two-sided log-rank test stratified by ECOG performance status, number of prior regimens, prior platinum, best response to prior chemotherapy.
Figure 3 depicts the Kaplan-Meier curves for overall survival.
Figure 3: Kaplan-Meier Curves for Overall Survival of Patients by Treatment Group in Study 4

14.4 NSCLC - Lack of Efficacy of Erlotinib Administered Concurrently with Chemotherapy

Results from two, multicenter, placebo-controlled, randomized, trials in over 1000 patients conducted in first-line patients with locally advanced or metastatic NSCLC showed no clinical benefit with the concurrent administration of erlotinib with platinum-based chemotherapy [carboplatin and paclitaxel (Erlotinib, N = 526) or gemcitabine and cisplatin (Erlotinib, N = 580)].

14.5 Pancreatic Cancer - Erlotinib Administered Concurrently with Gemcitabine

The efficacy and safety of erlotinib in combination with gemcitabine as a first-line treatment was assessed in Study 5, a randomized, double-blind, placebo-controlled trial in 569 patients with locally advanced, unresectable or metastatic pancreatic cancer. Patients were randomized 1:1 to receive erlotinib (100 mg or 150 mg) or placebo once daily on a continuous schedule plus gemcitabine by intravenous infusion (1000 mg/m^2, Cycle 1 - Days 1, 8, 15, 22, 29, 36 and 43 of an 8-week cycle; Cycle 2 and subsequent cycles - Days 1, 8 and 15 of a 4-week cycle [the approved dose and schedule for pancreatic cancer, see the gemcitabine package insert]). Erlotinib or placebo was taken orally once daily until disease progression or unacceptable toxicity. The primary endpoint was survival. Secondary endpoints included response rate, and progression-free survival (PFS). Duration of response was also examined. The study was conducted in 18 countries. A total of 285 patients were randomized to receive gemcitabine plus erlotinib (261 patients in the 100 mg cohort and 24 patients in the 150 mg cohort) and 284 patients were randomized to receive gemcitabine plus placebo (260 patients in the 100 mg cohort and 24 patients in the 150 mg cohort). Too few patients were treated in the 150 mg cohort to draw conclusions.

In the 100 mg cohort, baseline demographics of the overall study population were as follows: male (52%), white (88%), Asian (7%), black (2%), age < 65 years (53%), ECOG PS 1 (51%), ECOG PS 0 (32%), and ECOG PS 2 (17%). There was a slightly larger proportion of females in the erlotinib arm (51%) compared with the placebo arm (44%). The median time from initial diagnosis to randomization was approximately 1.0 month. The majority of the patients (76%) had distant metastases at baseline and 24% had locally advanced disease.
The results of the study are shown in Table 9.
Table 9: Efficacy Results: Erlotinib 100 mg Cohort (Study 5)

Efficacy Parameter | Erlotinib + Gemcitabine (N = 261) | Placebo + Gemcitabine (N = 260)
Overall Survival (OS)
Number of Deaths | 250 | 254
Median OS in Months (95% CI) | 6.5 (6.0, 7.4) | 6.0 (5.1, 6.7)
Hazard Ratio (95% CI)(1) | 0.81 (0.68, 0.97)
p-value (stratified log-rank test)(2) | 0.028
Progression-Free Survival (PFS)
Number of Progression or Deaths (%) | 225 | 232
Median PFS in Months (95% CI) | 3.8 (3.6, 4.9) | 3.6 (3.3, 3.8)
Hazard Ratio (95% CI)^1 | 0.76 (0.64, 0.92)
Objective Response
Objective Response Rate (95% CI) | 8.6% (5.4, 12.9) | 7.9% (4.8, 12.0)

(1)Cox regression model with the following covariates: ECOG performance status and extent of disease.
(2)Two-sided log-rank test stratified by ECOG performance status and extent of disease.
Survival was evaluated in the intent-to-treat population. Figure 4 depicts the Kaplan-Meier curves for overall survival in the 100 mg cohort. The primary survival and PFS analyses were two-sided log-rank tests stratified by ECOG performance status and extent of disease
Figure 4: Kaplan-Meier Curves for Overall Survival: 100 mg Cohort in Study 5

Note:HR is from Cox regression model with the following covariates: ECOG performance status and extent of disease. The p-value is from two-sided Log-Rank test stratified by ECOG performance status and extent of disease.

16 HOW SUPPLIED/STORAGE AND HANDLING

Erlotinib tablets, 25 mg: White colored, round biconvex film-coated tablets debossed with “H” on one side and “28” on the other side. They are supplied in:
Bottle of 30 tablets (NDC 31722-263-30)
Erlotinib tablets, 100 mg: White colored, round biconvex film-coated tablets debossed with “H” on one side and “21” on the other side. They are supplied in:
Bottle of 30 tablets (NDC 31722-264-30)
Erlotinib tablets, 150 mg: White colored, round biconvex film-coated tablets debossed with “H” on one side and “22” on the other side. They are supplied in:
Bottle of 30 tablets (NDC 31722-265-30)
Store at 20°C to 25°C (68°F to 77°F) [see USP Controlled Room Temperature].

17 PATIENT COUNSELING INFORMATION

Skin rash, bullous and exfoliative skin disorders
• Advise patients that skin reactions can occur or worsen on sun-exposed areas while taking erlotinib tablets, and proactive intervention may include alcohol-free emollient cream and use of sunscreen or avoidance of sun exposure. Advise patients that hyperpigmentation or dry skin, with or without digital skin fissures, have been reported and in the majority of cases were associated with rash [see Adverse Reactions (6.1)].
• Advise patients that erlotinib tablets can increase the risk of bullous and exfoliative skin disorders and to seek immediately medical attention for severe skin reactions [see Warnings and Precautions (5.5)].
Diarrhea
Advise patients that diarrhea can usually be managed with loperamide and to contact their healthcare provider for severe or persistent diarrhea [see Adverse Reactions (6.1)].
Interstitial lung disease
Advise patients of the risk of severe or fatal ILD, including pneumonitis. Advise patients to contact their healthcare provider immediately to report new of worsening unexplained shortness of breath or coughing [see Dosage and Administration (2.4) and Warnings and Precautions (5.1)].
Renal failure
Advise patients of the risk of developing renal failure. Inform patients of the need for the healthcare provider to monitor kidney function and electrolytes [see Warnings and Precautions (5.2)].
Hepatotoxicity
Advise patients to immediately report signs or symptoms of hepatotoxicity [see Warnings and Precautions (5.3)].
Gastrointestinal perforations
Advise patients that erlotinib tablets can increase the risk of gastrointestinal perforation or fistula and to seek immediate medical attention for severe abdominal pain [see Dosage and Administration (2.4) and Warnings and Precautions (5.4)].
Cerebrovascular accident
Advise patients of the risk of cerebrovascular accident and see immediate medical attention [see Dosage and Administration (2.4) and Warnings and Precautions (5.6)].
Ocular disorders

Advise patients promptly to contact their healthcare provider if they develop eye signs or symptoms, lacrimation, light sensitivity, blurred vision, eye pain, red eye, or changes in vision [see Dosage and Administration (2.4) and Warnings and Precautions (5.8)].
Hemorrhage in patients taking warfarin
Advise patients who are receiving warfarin of the need to monitor INR or other coumarin-derivative anticoagulants [see Warnings and Precautions (5.9) and Drug Interactions (7)].
Hair and nail disorders
Advise patients that hair and nail disorders, including hirsutism and brittle and loose nails, have been reported [see Adverse Reactions (6.1)].
Embryo-fetal toxicity
• Advise pregnant women and females of reproductive potential of the potential risk to a fetus. Advise females of reproductive potential to inform their healthcare provider of a known or suspected pregnancy [see Warnings and Precautions (5.10), Use in Specific Populations (8.1)] .
• Advise females of reproductive potential to use effective contraception during treatment with erlotinib tablets, and for 1 month after the last dose [see Use in Specific Populations (8.3)].
Lactation
• Advise women not to breastfeed during treatment with erlotinib tablets and for 2 weeks after the final dose [see Use in Specific Populations (8.2)].
Smoking
• Advise patients to contact their health care provider for any changes in smoking status and that the dose of erlotinib tablets may need to be adjusted if they smoke [see Drug Interactions (7) and Clinical Pharmacology (12.3)]
• Advise patients to stop smoking [see Clinical Pharmacology (12.3)].

Manufactured for:
Camber Pharmaceuticals, Inc.
Piscataway, NJ 08854

By: HETEROTM
Hetero Labs Limited, Unit V, Polepally, Jadcherla,
Mahabubnagar - 509 301, India.

Revised : 05/2024

PACKAGE LABEL.PRINCIPAL DISPLAY PANEL

Erlotinib Tablets 25 mg 30s Container Label

Erlotinib Tablets 25 mg 30s Carton Label

Erlotinib Tablets 100 mg 30s Container Label

Erlotinib Tablets 100 mg 30s Carton Label

Erlotinib Tablets 150 mg 30s Container Label

Erlotinib Tablets 150 mg 30s Carton Label